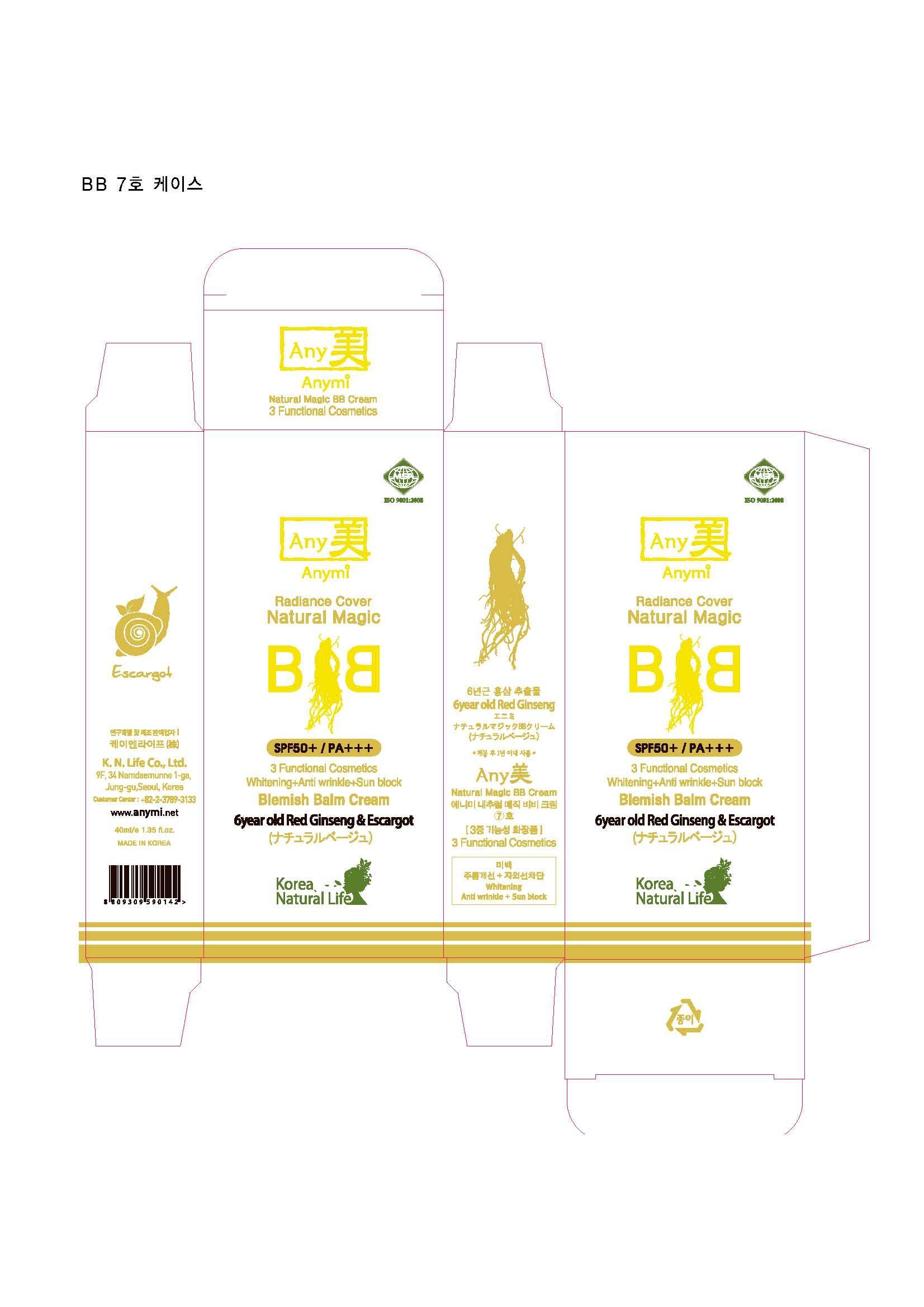 DRUG LABEL: Any Mi Natural Magic BB No.7
NDC: 62695-2001 | Form: CREAM
Manufacturer: K.N.Life Co., Ltd.
Category: otc | Type: HUMAN OTC DRUG LABEL
Date: 20140315

ACTIVE INGREDIENTS: ALLANTOIN 0.0005 g/1 mL
INACTIVE INGREDIENTS: WATER; GLYCERIN; CYCLOMETHICONE; PROPYLENE GLYCOL; ARBUTIN

Drug Facts

ACTIVE INGREDIENT

allantoin

INACTIVE INGREDIENT

water, cyclomethicone, titanium dioxide, zinc oxide, ethylhexyl methoxycinnamate, panax ginseng root ext, peg-7 dimethicone, propylene glycol, arbutin, bentonite, cetyl peg/ppg-10/1 dimethicone, hexyl laurate, betaine, polymethyl methacrylate, sodium chloride, etc

PURPOSE

whitening
anti-wrinkle
sun block

keep out of reach of the children

INDICATIONS AND USAGE

after foundation, apply small amounts to whole face by tapping until it is absorbed to skin completely

WARNINGS

1. if you have any abnormal symptoms as followings, you should discontinue to use this cream. In case of using continuously, you have to consult to dermatologist because it may make symptoms worse.
a. red macule, swelling, urtication, and irritation during use
b. symptoms like above by direct ray
2. do not use if you have a wound, eczema, and dermatitis to the area where you apply this cream
3. caution during storing and handling
a. close the cap after use
b. keep it to the area where babies and infants cannot reachto
c. keep it to the area where has not high or low temperature and has no direct ray

DOSAGE AND ADMINISTRATION

for external use only